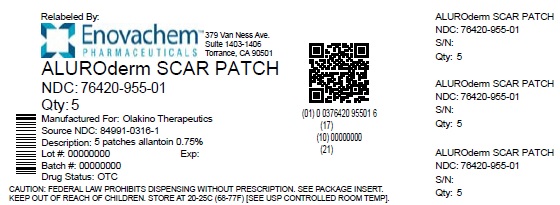 DRUG LABEL: Aluroderm Scar
NDC: 76420-955 | Form: PATCH
Manufacturer: Asclemed USA, Inc.
Category: otc | Type: HUMAN OTC DRUG LABEL
Date: 20250401

ACTIVE INGREDIENTS: ALLANTOIN 0.0075 g/1 g
INACTIVE INGREDIENTS: CARBOXYMETHYLCELLULOSE SODIUM; HYALURONIC ACID; TAXIFOLIN; POLYURETHANE-39

Aluroderm Scar Patch

ACTIVE INGREDIENTS

Allantoin 0.75%

PURPOSE

Skin Protectant

USES

-Scar Management

-Temporarily protects and helps relieve chapped or cracked skin

WARNINGS

FOR EXTERNAL USE ONLY

DO NOT USE

-On deep punctures, serious burns, or infected skin

WHEN USING THIS PRODUCT

Avoid contact with the eyes

STOP USE AND ASK DOCTOR IF

-Condition worsens

-Excessive skin irritation develops

-Condition persists for more than 7 days, or condition clears up and occurs again within 3 days

IF PREGNANT OR BREASTFEEDING

Consult a physician before use

KEEP OUT OF REACH OF CHILDREN

If ingested, seek medical help or contact Poison Control immediately

DIRECTIONS

Adults and Children 12 Years of Age and Older

-Clean and dry the affected area

-Apply as needed

OTHER INFORMATION

-Store at room temperature

INACTIVE INGREDIENTS

Hyaluronic Acid, Taxifolin, Polyurethane, Sodium Carboxymethyl Cellulose

QUESTIONS OR COMMENTS

info@olakinotherapeutics.com

PACKAGE LABEL

Relabeled by:

Enovachem PHARMACEUTICALS

Torrance, CA 90501